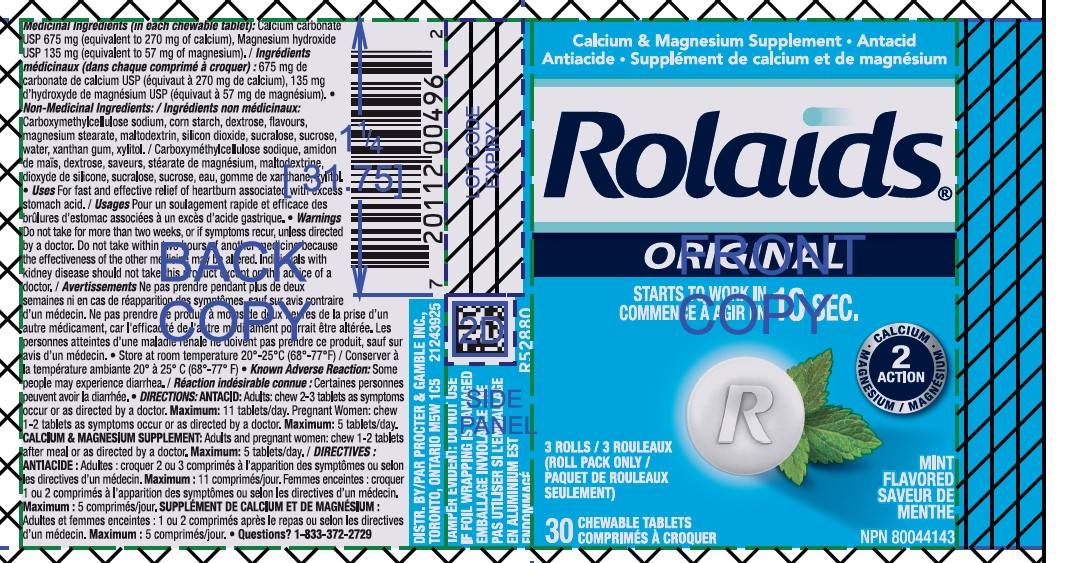 DRUG LABEL: Calcium Carbonate, Magnesium Hydroxide
NDC: 10267-0040 | Form: TABLET, CHEWABLE
Manufacturer: Contract Pharmacal Corp.
Category: otc | Type: HUMAN OTC DRUG LABEL
Date: 20250612

ACTIVE INGREDIENTS: CALCIUM CARBONATE 675 mg/1 1; MAGNESIUM HYDROXIDE 135 mg/1 1
INACTIVE INGREDIENTS: XYLITOL; ACACIA; CARBOXYMETHYLCELLULOSE; MALTODEXTRIN; SUCRALOSE; DEXTROSE; STARCH, CORN; XANTHAN GUM; MAGNESIUM STEARATE; SUCROSE; SILICON DIOXIDE

5761- Export